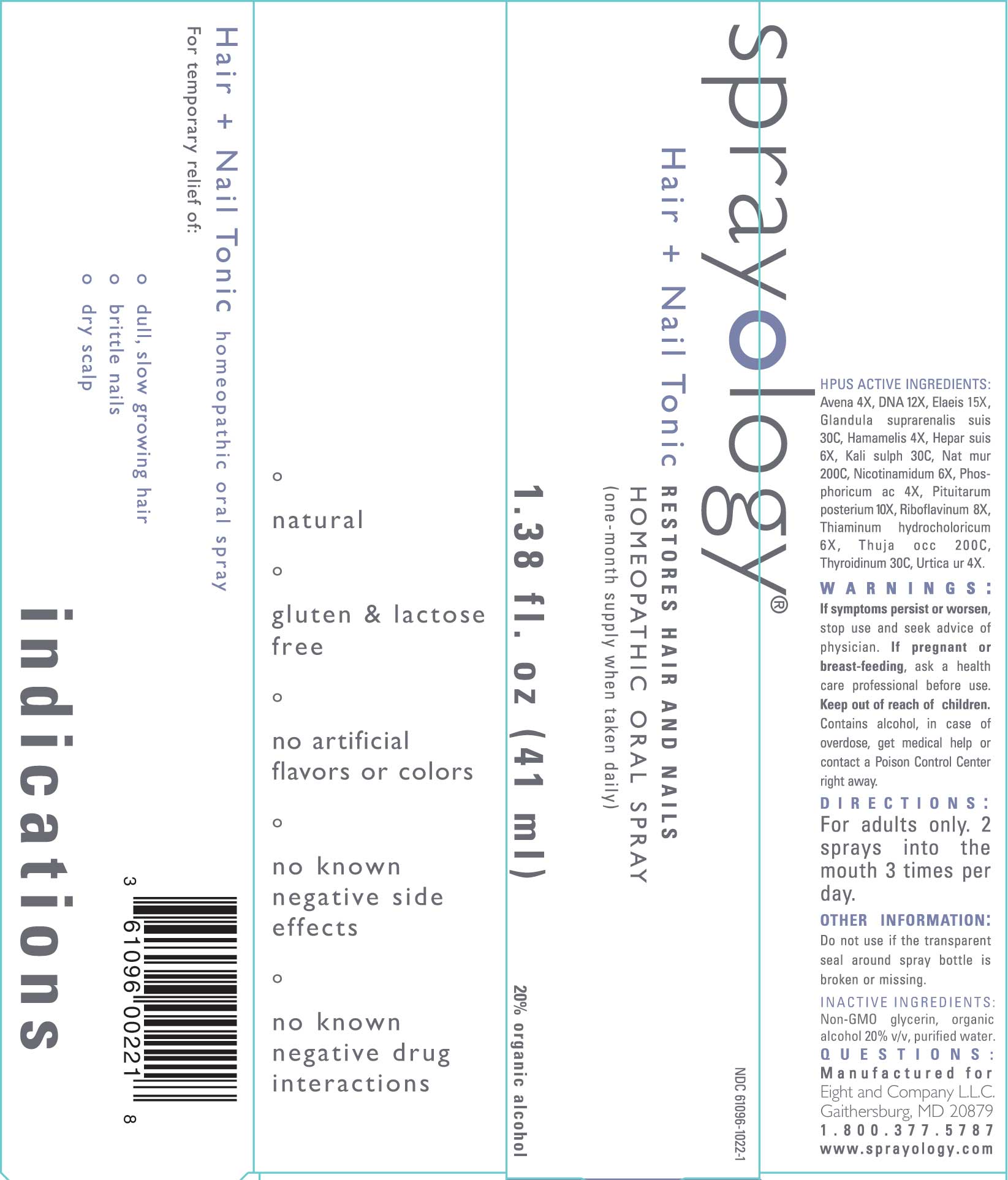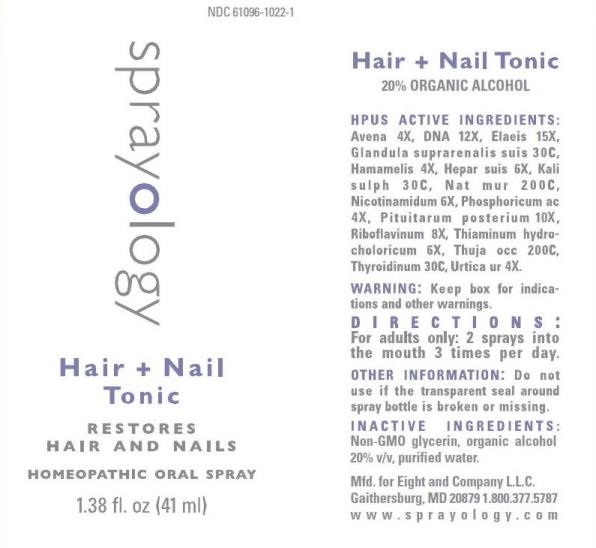 DRUG LABEL: Hair and Nail Tonic
NDC: 61096-1022 | Form: LIQUID
Manufacturer: Eight and Company L.L.C
Category: homeopathic | Type: HUMAN OTC DRUG LABEL
Date: 20251218

ACTIVE INGREDIENTS: AVENA SATIVA FLOWERING TOP 4 [hp_X]/41 mL; HERRING SPERM DNA 12 [hp_X]/41 mL; ELAEIS GUINEENSIS FRUIT 15 [hp_X]/41 mL; SUS SCROFA ADRENAL GLAND 30 [hp_C]/41 mL; HAMAMELIS VIRGINIANA ROOT BARK/STEM BARK 4 [hp_X]/41 mL; PORK LIVER 6 [hp_X]/41 mL; POTASSIUM SULFATE 30 [hp_C]/41 mL; SODIUM CHLORIDE 200 [hp_C]/41 mL; NIACINAMIDE 6 [hp_X]/41 mL; PHOSPHORIC ACID 4 [hp_X]/41 mL; SUS SCROFA PITUITARY GLAND 10 [hp_X]/41 mL; RIBOFLAVIN 8 [hp_X]/41 mL; THIAMINE HYDROCHLORIDE 6 [hp_X]/41 mL; THUJA OCCIDENTALIS LEAFY TWIG 200 [hp_C]/41 mL; THYROID, UNSPECIFIED 30 [hp_C]/41 mL; URTICA URENS WHOLE 4 [hp_X]/41 mL
INACTIVE INGREDIENTS: GLYCERIN; ALCOHOL; WATER

Hair and Nail Tonic

ACTIVE INGREDIENTS:

Avena sativa 4X, DNA 12X, Elaeis 15X, Glandula suprarenalis suis 30C, Hamamelis 4X, Hepar suis 6X, Kali sulph 30C, Nat mur 200C, Nicotinamidum 6X, Phosphoricum ac 4X, Pituitarum posterium 10X, Riboflavinum 8X, Thiaminum hydrochloricum 6X, Thuja occ 200C, Thyroidinum 30C, Urtica urens 4X.

PURPOSE:

For temporary relief of:

° dull, slow growing hair
° brittle nails
° dry scalp

WARNINGS:

If symptoms persist or worsen, stop use and seek advice of physician. If pregnant or breast-feeding, ask a health care professional before use. Keep out of reach of children. Contains alcohol, in case of overdose, get medical help or contact a Poison Control Center right away.

Keep out of reach of children. Contains alcohol, in case of overdose, get medical help or contact a Poison Control Center right away.

DIRECTIONS:

For adults only, 2 sprays into the mouth 3 times per day.

OTHER INFORMATION:

Do not use if the transparent seal around spray bottle is broken or missing.

INDICATIONS:

For temporary relief of:

° dull, slow growing hair

° brittle nails

° dry scalp

° natural

° gluten & lactose free

° no artificial flavors or colors

° no known negative side effects

° no known negative drug interactions

INACTIVE INGREDIENTS:

Non-GMO glycerin, organic alcohol 20% v/v, purified water.

QUESTIONS:

Mfd. for Eight and Company L.L.C.

Gaithersburg, MD 20879 1.800.377.5787

www.sprayology.com

PACKAGE LABEL DISPLAY:

sprayology

Hair + Nail Tonic

RESTORES HAIR AND NAILS

HOMEOPATHIC ORAL SPRAY

1.38 fl. oz (41 ml)